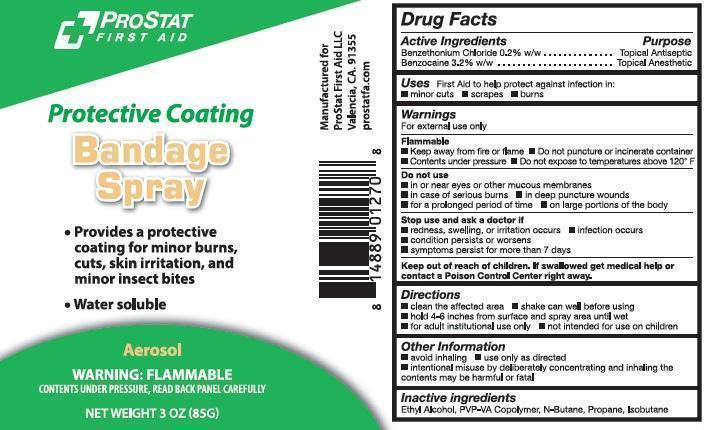 DRUG LABEL: ProStat Protective Coating Bandage First Aid
NDC: 58228-0102 | Form: AEROSOL, SPRAY
Manufacturer: ProStat First Aid
Category: otc | Type: HUMAN OTC DRUG LABEL
Date: 20140224

ACTIVE INGREDIENTS: BENZETHONIUM CHLORIDE 170 mg/85 g; BENZOCAINE 2720 mg/85 g
INACTIVE INGREDIENTS: ALCOHOL; ISOBUTANE; BUTANE; PROPANE; COPOVIDONE K25-31

ProStat Bandage Spray

Active ingredients

Benzethonium Chloride 0.2% w/w
Benzocaine 3.2% w/w

Purpose

Topical antiseptic
Topical anesthetic

Uses

First aid to help protect against infection in

minor cuts
scrapes
burns

Warnings

For external use only

Flammable
keep away from fire or flame
contents under pressure
do not puncture or incinerate container
do not expose to temperatures above 120° F

Do not use

in or near eyes or other mucous membranes
in case of serious burns
in deep puncture wounds
for a prolonged period of time
on large portions of the body

Stop use and ask a doctor if

redness, swelling, or irritation occurs
infection occurs
condition persists or worsens
symptoms persist for more than 7 days

Directions

clean the affected area
shake can well before using
hold 4-6 inches from surface and spray area until wet
for adult institutional use only
not intended for use on children

Other information

avoid inhaling
use only as directed
intentional misuse by deliberately concentrating and inhaling contents may be harmful or fatal

Inactive ingredients

Ethyl alcohol, PVP-VA copolymer, N-Butane, Propane, Isobutane